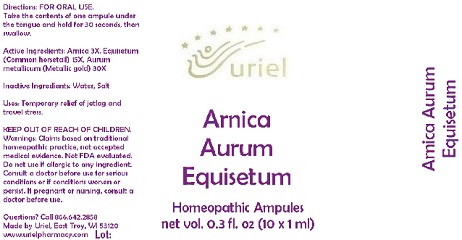 DRUG LABEL: Arnica Aurum Equisetum
NDC: 48951-1111 | Form: LIQUID
Manufacturer: Uriel Pharmacy Inc.
Category: homeopathic | Type: HUMAN OTC DRUG LABEL
Date: 20180416

ACTIVE INGREDIENTS: ARNICA MONTANA 3 [hp_X]/1 mL; EQUISETUM ARVENSE TOP 15 [hp_X]/1 mL; GOLD 30 [hp_X]/1 mL
INACTIVE INGREDIENTS: SODIUM CHLORIDE; WATER

Arnica Aurum Equisetum

INDICATIONS AND USAGE

Directions: FOR ORAL USE.

DOSAGE AND ADMINISTRATION

Take the contents of one ampule under the tongue and hold for 30 seconds, then swallow.

ACTIVE INGREDIENT

Active Ingredients: Arnica 3X, Equisetum (Common horsetail) 15X, Aurum metallicum (Metallic gold) 30X

Inactive Ingredients: Water, Salt

PURPOSE

Uses: Temporary relief of jetlag and travel stress.

KEEP OUT OF REACH OF CHILDREN.

WARNINGS

Warnings: Claims based on traditional homeopathic practice, not accepted medical evidence. Not FDA evaluated. Do not use if allergic to any ingredient. Consult a doctor before use for serious conditions or if conditions worsen or persist. If pregnant or nursing, consult a doctor before use.

QUESTIONS

Questions? Call 866.642.2858 Made by Uriel, East Troy, WI 53120 www.urielpharmacy.com